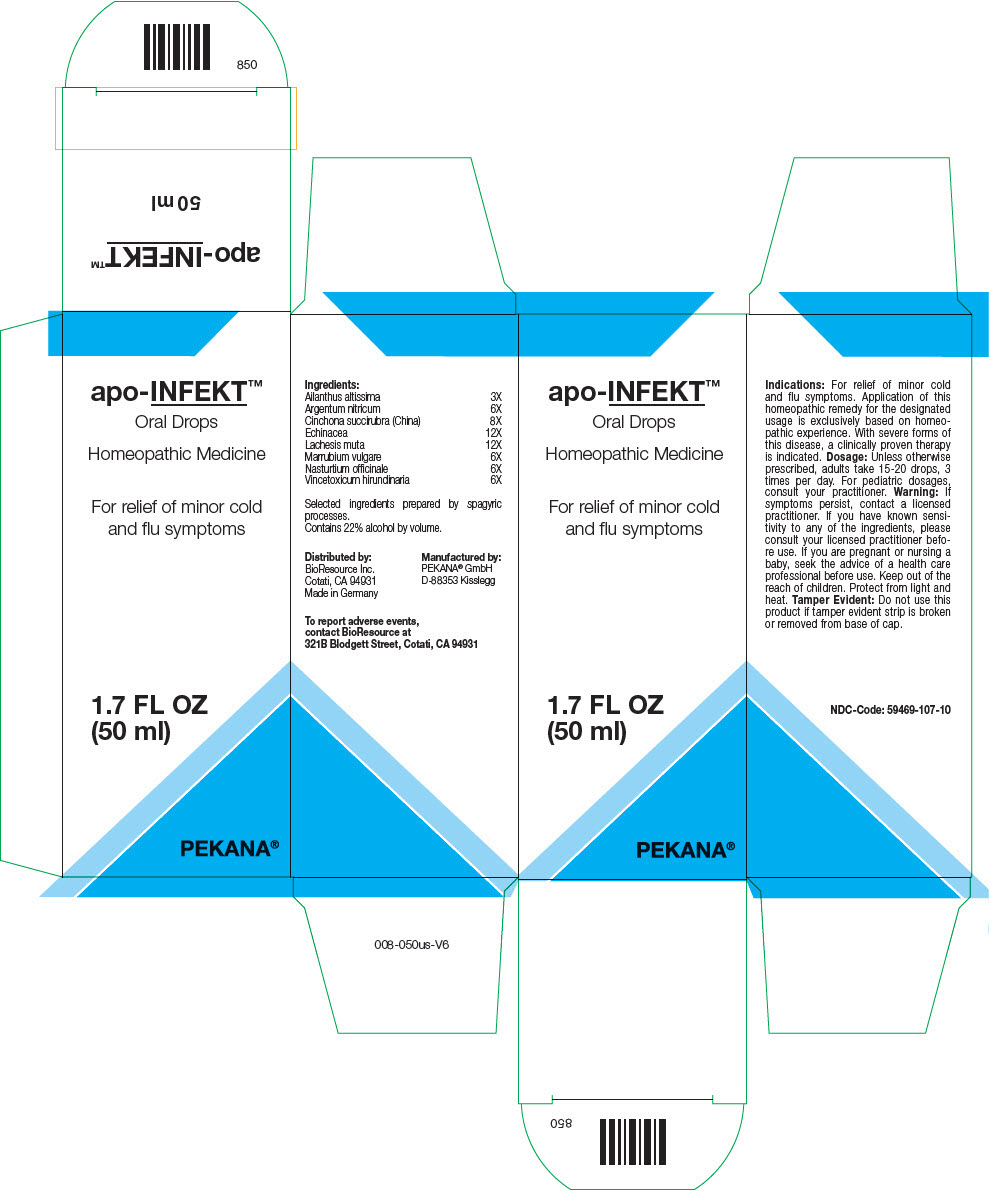 DRUG LABEL: apo-INFEKT
NDC: 59469-107 | Form: SOLUTION/ DROPS
Manufacturer: PEKANA Naturheilmittel GmbH
Category: homeopathic | Type: HUMAN OTC DRUG LABEL
Date: 20221205

ACTIVE INGREDIENTS: Ailanthus altissima Whole 3 [hp_X]/50 mL; Silver Nitrate 6 [hp_X]/50 mL; Cinchona Officinalis Bark 8 [hp_X]/50 mL; Lachesis Muta Venom 12 [hp_X]/50 mL; VINCETOXICUM HIRUNDINARIA LEAF 6 [hp_X]/50 mL; Echinacea, unspecified 12 [hp_X]/50 mL; MARRUBIUM VULGARE WHOLE 6 [hp_X]/50 mL; Nasturtium officinale Whole 6 [hp_X]/50 mL
INACTIVE INGREDIENTS: Water; Alcohol

apo-INFEKT™

ACTIVE INGREDIENT

Ingredients:
Ailanthus altissima | 3X
Argentum nitricum | 6X
Cinchona succirubra (China) | 8X
Echinacea | 12X
Lachesis muta | 12X
Marrubium vulgare | 6X
Nasturtium officinale | 6X
Vincetoxicum hirundinaria | 6X

Selected ingredients prepared by spagyric processes.

INACTIVE INGREDIENT

Contains 22% alcohol by volume.

Indications

PURPOSE

For relief of minor cold and flu symptoms. Application of this homeopathic remedy for the designated usage is exclusively based on homeopathic experience. With severe forms of this disease, a clinically proven therapy is indicated.

Dosage

Unless otherwise prescribed, adults take 15-20 drops, 3 times per day. For pediatric dosages, consult your practitioner.

Warning

If symptoms persist, contact a licensed practitioner. If you have known sensitivity to any of the ingredients, please consult your licensed practitioner before use. If you are pregnant or nursing a baby, seek the advice of a health care professional before use.

Keep out of the reach of children.

STORAGE AND HANDLING

Protect from light and heat.

Tamper Evident

Do not use this product if tamper evident strip is broken or removed from base of cap.

QUESTIONS

To report adverse events, contact BioResource at 321B Blodgett Street, Cotati, CA 94931

Distributed by:
BioResource Inc.
Cotati, CA 94931

Manufactured by:
PEKANA® GmbH
D-88353 Kisslegg

PRINCIPAL DISPLAY PANEL - 50 ml Bottle Box

apo-INFEKT™
Oral Drops

Homeopathic Medicine

For relief of minor cold
and flu symptoms

1.7 FL OZ
(50 ml)

PEKANA®